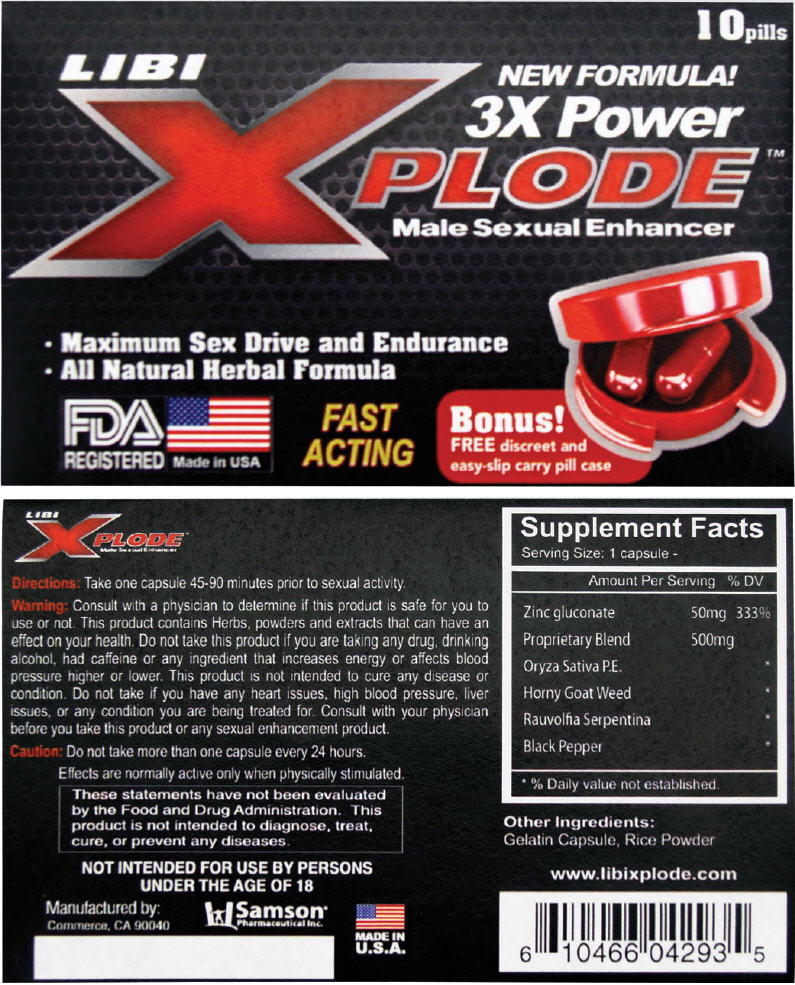 DRUG LABEL: Libi Xplode Male Sexual Enhancer
NDC: 20146-1001 | Form: CAPSULE
Manufacturer: SAMSON PHARMACEUTICAL
Category: other | Type: DIETARY SUPPLEMENT
Date: 20160408

ACTIVE INGREDIENTS: Zinc Gluconate 50 mg/1 1
INACTIVE INGREDIENTS: Brown Rice; Icariin; Rauwolfia Serpentina; Black Pepper

Libi Xplode™ Male Sexual Enhancer

Directions

Take one capsule 45-90 minutes prior to sexual activity.

Warning

Consult with a physician to determine if this product is safe for you to use or not. This product contains Herbs, powders and extracts that can have an effect on your health. Do not take this product if you are taking any drug, drinking alcohol, had caffeine or any ingredient that increases energy or affects blood pressure higher or lower. This product is not intended to cure any disease or condition. Do not take if you have any heart issues, high blood pressure, liver issues, or any condition you are being treated for. Consult with your physician before you take this product or any sexual enhancement product.

Caution

Do not take more than one capsule every 24 hours.

HEALTH CLAIM

These statements have not been evaluated by the Food and Drug Administration. This product is not intended to diagnose, treat, cure, or prevent any diseases. Not intended for use by person under the age of 18.

HEALTH CLAIM

Supplement Facts
Serving Size: 1 capsule
Amount Per Serving |  | % DV
Zinc gluconate | 50 mg | 333%
Proprietary Blend | 500 mg
Oryza Sativa P.E. |  | [% Daily value not established.]
Horny Goat Weed
RauvolfiaSerpentina
Black Pepper

Other Ingredients

Gelatin Capsule, Rice Powder

HEALTH CLAIM

Manufactured by:
Samson®
Pharmaceutical Inc.
Commerce, CA 90040

PRINCIPAL DISPLAY PANEL - 10 Capsule Blister Pack Box

10pills

NEW FORMULA!
3X Power
LIBI
XPLODE™
Male Sexual Enhancer

- Maximum Sex Drive and Endurance
- All Natural Herbal Formula

FDA
REGISTERED
Made in USA

FAST
ACTING

Bonus!
FREE discreet and
easy-slip carry pill case